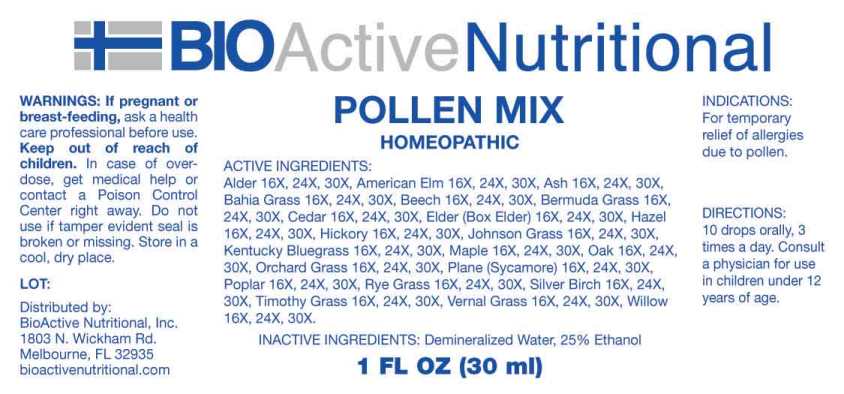 DRUG LABEL: Pollen Mix
NDC: 43857-0535 | Form: LIQUID
Manufacturer: BioActive Nutritional, Inc.
Category: homeopathic | Type: HUMAN OTC DRUG LABEL
Date: 20241017

ACTIVE INGREDIENTS: ULMUS AMERICANA POLLEN 16 [hp_X]/1 mL; PLATANUS X ACERIFOLIA POLLEN 16 [hp_X]/1 mL; FRAXINUS EXCELSIOR POLLEN 16 [hp_X]/1 mL; FAGUS SYLVATICA POLLEN 16 [hp_X]/1 mL; SALIX X FRAGILIS POLLEN 16 [hp_X]/1 mL; SAMBUCUS CANADENSIS FLOWER 16 [hp_X]/1 mL; ALNUS RUBRA POLLEN 16 [hp_X]/1 mL; JUNIPERUS VIRGINIANA POLLEN 16 [hp_X]/1 mL; ACER SACCHARUM POLLEN 16 [hp_X]/1 mL; CORYLUS AVELLANA POLLEN 16 [hp_X]/1 mL; POPULUS ALBA POLLEN 16 [hp_X]/1 mL; POA PRATENSIS POLLEN 16 [hp_X]/1 mL; DACTYLIS GLOMERATA POLLEN 16 [hp_X]/1 mL; BETULA PENDULA POLLEN 16 [hp_X]/1 mL; CYNODON DACTYLON POLLEN 16 [hp_X]/1 mL; SORGHUM HALEPENSE POLLEN 16 [hp_X]/1 mL; SECALE CEREALE POLLEN 16 [hp_X]/1 mL; ANTHOXANTHUM ODORATUM POLLEN 16 [hp_X]/1 mL; PASPALUM NOTATUM POLLEN 16 [hp_X]/1 mL; QUERCUS ROBUR POLLEN 16 [hp_X]/1 mL; CARYA GLABRA POLLEN 16 [hp_X]/1 mL; PHLEUM PRATENSE POLLEN 16 [hp_X]/1 mL
INACTIVE INGREDIENTS: WATER; ALCOHOL

DRUG FACTS:

ACTIVE INGREDIENTS:

American Elm 16X, 24X, 30X, Plane (Sycamore) 16X, 24X, 30X, Ash 16X, 24X, 30X, Beech 16X, 24X, 30X, Willow 16X, 24X, 30X, Elder (Box Elder) 16X, 24X, 30X, Alder 16X, 24X, 30X, Cedar 16X, 24X, 30X, Maple 16X, 24X, 30X, Hazel 16X, 24X, 30X, Poplar 16X, 24X, 30X, Kentucky Bluegrass 16X, 24X, 30X, Orchard Grass 16X, 24X, 30X, Silver Birch 16X, 24X, 30X, Bermuda Grass 16X, 24X, 30X, Johnson Grass 16X, 24X, 30X, Rye Grass 16X, 24X, 30X, Vernal Grass 16X, 24X, 30X, Bahia Grass 16X, 24X, 30X, Oak 16X, 24X, 30X, Hickory 16X, 24X, 30X, Timothy Grass 16X, 24X, 30X.

INDICATIONS:

For temporary relief of allergies due to pollen.

WARNINGS:

If pregnant or breast-feeding, ask a health care professional before use.

Keep out of reach of children. In case of overdose, get medical help or contact a Poison Control Center right away.

Do not use if tamper evident seal is broken or missing.

Store in cool, dry place.

Keep out of reach of children. In case of overdose, get medical help or contact a Poison Control Center right away.

DIRECTIONS:

10 drops orally, 3 times a day. Consult a physician for use in children under 12 years of age.

INDICATIONS:

For temporary relief of allergies due to pollen.

INACTIVE INGREDIENTS:

Demineralized Water, 25% Ethanol

QUESTIONS:

Distributed by:

BioActive Nutritional, Inc.

1803 N. Wickham Rd.

Melbourne, FL 32935

bioactivenutritional.com

PACKAGE LABEL DISPLAY:

BIOActive Nutritional

POLLEN MIX

HOMEOPATHIC

1 FL OZ (30 ml)